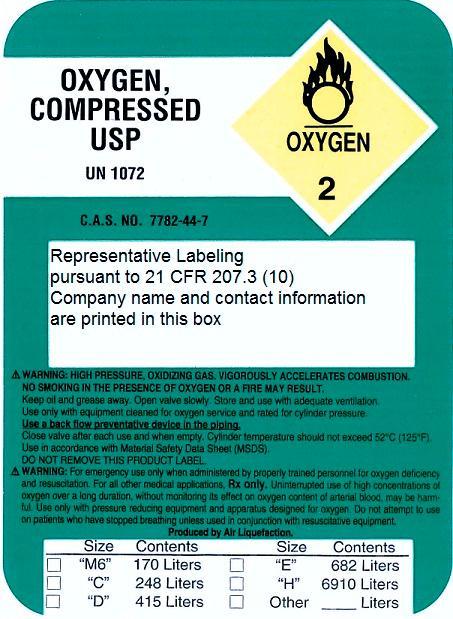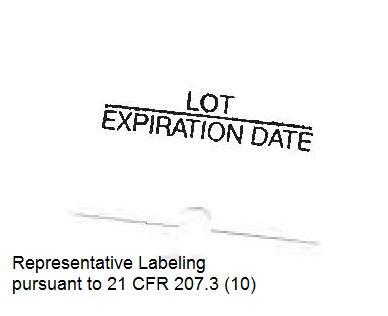 DRUG LABEL: Oxygen
NDC: 5575-0001 | Form: GAS
Manufacturer: Ecumed Inc dba Aronson Medical
Category: prescription | Type: HUMAN PRESCRIPTION DRUG LABEL
Date: 20251028

ACTIVE INGREDIENTS: OXYGEN 99 L/100 L

Oxygen

Principal for Oxygen Product

OXYGEN, COMPRESSED USP
UN 1072
C.A.S No. 7782-44-7
WARNING: HIGH PRESSURE, OXIDIZING GAS, VIGOROUSLY ACCELERATES COMBUSTION.
Keep oil and grease away. Open valve slowly. Store and use with adequate ventilation.
Use only with equipment cleaned for oxygen service and rated for cylinder pressure.
Use a back flow preventative device in the piping.
Close valve after each use and when empty. Cylinder temperatures should not exceed 52°C (125°F).
Use in accordance with Material Safety Data Sheet (MSDS).
DO NOT REMOVE THIS PRODUCT LABEL.

WARNING:

For emergency use only when administered by properly trained
personnel for oxygen deficiency and resuscitation. For all other
medical applications, Rx only.

Uninterrupted use of high concentrations of oxygen over a long
duration, without monitoring its effect on oxygen content of arterial
blood, may be harmful. Use only with pressure reducing equipment
and apparatus designed for oxygen. Do not attempt to use on
patients who have stopped breathing, unless used in conjunction
with resuscitative equipment.

Produced by Air Liquefaction